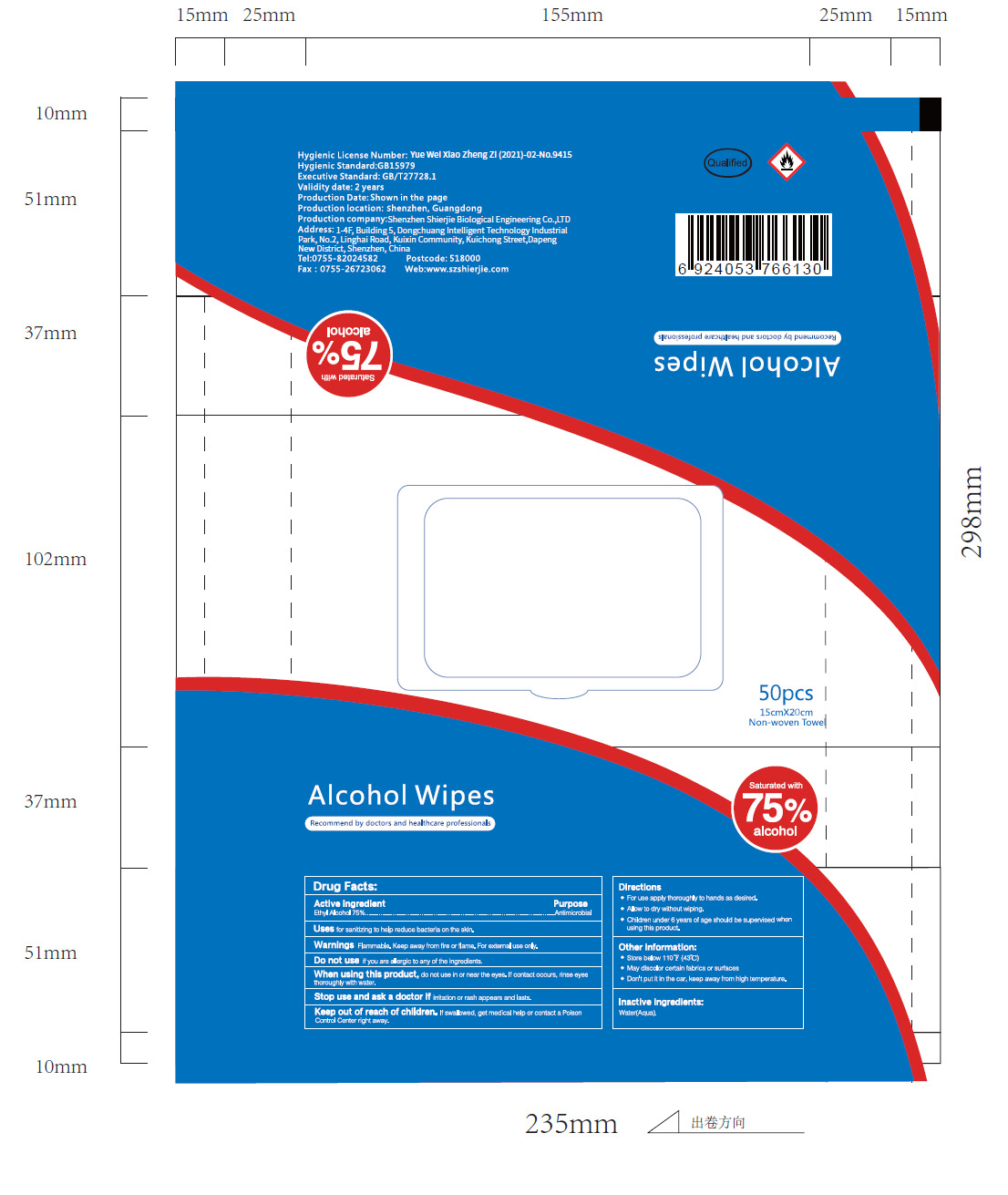 DRUG LABEL: Alcohol Wipes
NDC: 43116-050 | Form: CLOTH
Manufacturer: Shenzhen Shierjie Biological Engineering Co., LTD
Category: otc | Type: HUMAN OTC DRUG LABEL
Date: 20251127

ACTIVE INGREDIENTS: ALCOHOL 75 U/100 U
INACTIVE INGREDIENTS: WATER

43116-050

Active Ingredient

Ethyl Alcohol 75%

Purpose

Antimicrobial

Use

Uses for sanitizing to help reduce bacteria on the skin.

Warnings

Warnings Flammable. Keep away from fire or flame. For external use only.

Do not use if you are allergic to any of the ingredients.

When Using

When using this product, do not use in or near the eyes. If contact occurs, rinse eyes
thoroughly with water.

Stop Use

Stop use and ask a doctor if irritation or rash appears and lasts.

Keep Oot Of Reach Of Children

Keep out of reach of children. if swallowed., get medical help or contact a Poison Control Center right away.

Directions

●For use apply thoroughly to hands as desired.
●Allow to dry without wiping.
●Children under 6 years of age should be supervised when using this product.

Other information

●Store below 110F (43"C)
●May discolor certain fabrics or surfaces
●Don't put it in the car, keep away from high temperature.

Inactive ingredients

Water(Aqua).